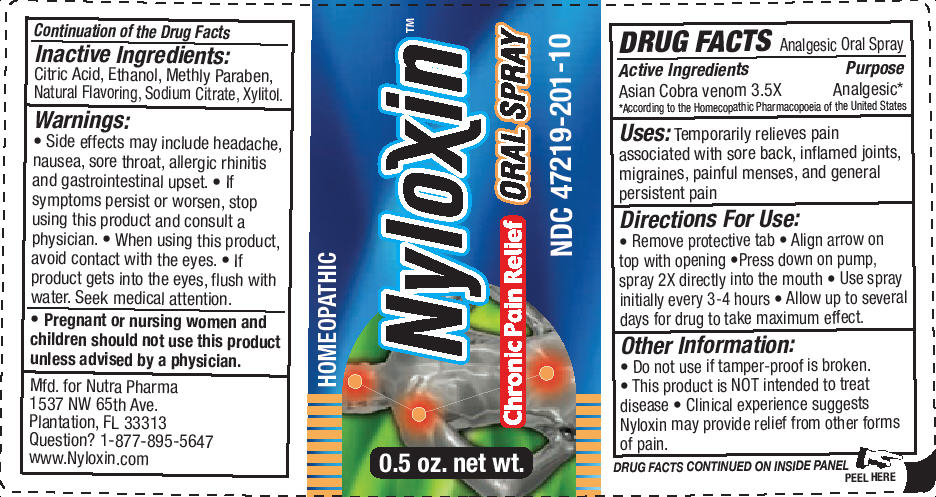 DRUG LABEL: NYLOXIN
NDC: 47219-202 | Form: SPRAY, METERED
Manufacturer: RECEPTOPHARM INC
Category: homeopathic | Type: HUMAN OTC DRUG LABEL
Date: 20091130

ACTIVE INGREDIENTS: NAJA NAJA VENOM .100 mg/1 mL
INACTIVE INGREDIENTS: ANHYDROUS CITRIC ACID; ANHYDROUS TRISODIUM CITRATE; METHYLPARABEN; XYLITOL; 2-(DIETHYLAMINO)ETHANOL

DRUG FACTS

Active Ingredients

Asian Cobra venom 3.5X

Purpose

Analgesic [According to the Homecopathic Pharmacopoeia of the United States]

INDICATIONS AND USAGE

Uses: Temporarily relieves pain associated with sore back, inflamed joints, migraines, painful menses, and general presistent pain

Directions For Use:

- Remove protective tab
- Align arrow on top with opening
- Press down on pump, spray 2X directly into the mouth
- Use spray initially every 3-4 hours
- Allow up to several days for drug to take maximum effect.

Other Information:

- Do not use if tamper-proof is broken.
- This product is NOT intended to treat disease
- Clinical experience suggests Nyloxin may provide relief from other forms of pain.

Inactive Ingredients:

Citric Acid, Ethanol, Methyl Paraben, Natural Flavoring, Sodium Citrate, Xylitol.

Warnings:

- Side effects may include headahce, nausea, sore throat, allergic rhinitis and gastointestinal upset.
- If symptoms persist or worsen, stop using this product and consult a physician.
- When using this product, avoid contact with the eyes.
- If product gets into the eyes, flush with water. Seek medical attention.

- Pregnant or nursing women and children should not use this product unless advised by a physician.

Mfd. for Nutra Pharma
1537 NW 65th Ave.
Plantation, FL 33313
Question? 1-877-895-5647
www.Nyloxin.com

PACKAGE LABEL

Package Label - Principal Display Panel – 0.5 oz Spray Label